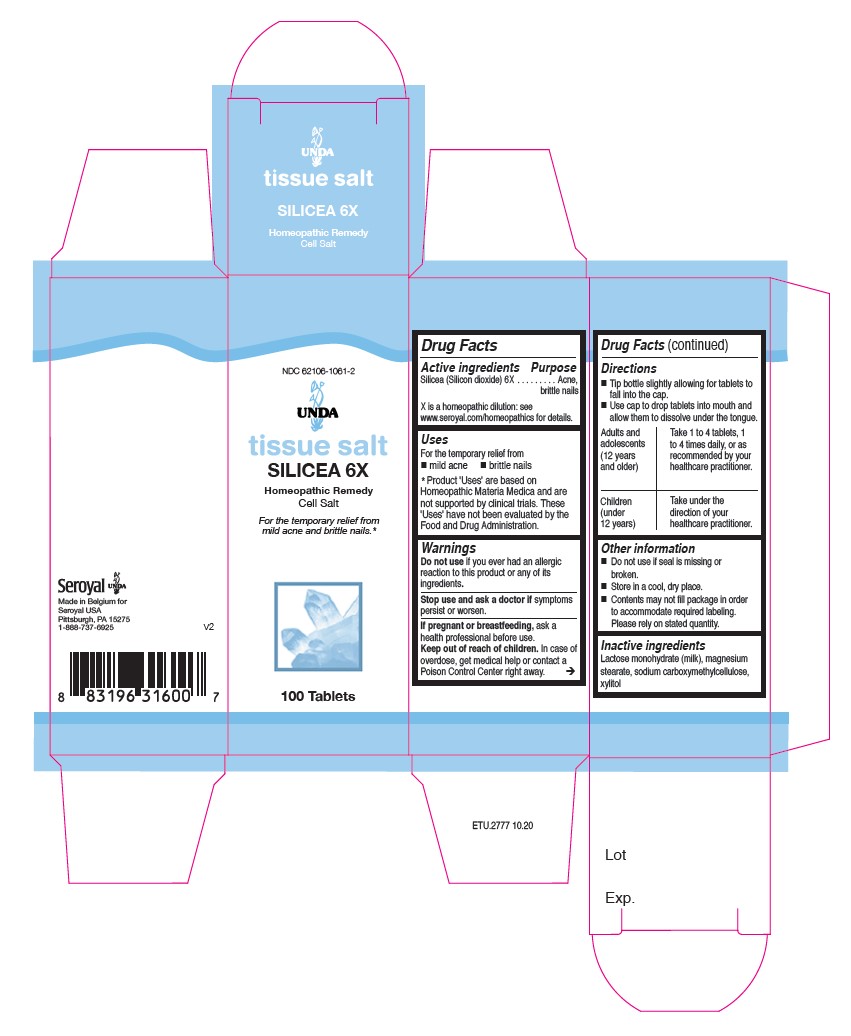 DRUG LABEL: SILICEA 6X
NDC: 62106-1061 | Form: TABLET
Manufacturer: Seroyal USA
Category: homeopathic | Type: HUMAN OTC DRUG LABEL
Date: 20210714

ACTIVE INGREDIENTS: SILICON DIOXIDE 6 [hp_X]/1 1
INACTIVE INGREDIENTS: LACTOSE MONOHYDRATE; XYLITOL; CROSCARMELLOSE SODIUM; MAGNESIUM STEARATE

SILICEA 6X

Active Ingredients

Silicea (Silicon dioxide) 6X

Uses

For the temporary relief from mild acne and brittle nails

Warnings

Do not use if you ever had an allergic reaction to this product or any of its ingredients.

Stop use and ask a doctor if symptoms persist or worsen.
If you are pregnant or breastfeeding, ask a healthcare practitioner before use.
Keep out of reach of children.
In case of overdose, get medical help or contact a Poison Control Center right away.

PREGNANCY OR BREAST FEEDING

If you are pregnant or breastfeeding, ask a healthcare practitioner before use.

Keep out of reach of children.

OVERDOSAGE

In case of overdose, get medical help or contact a Poison Control Center right away.

Stop use and ask a doctor if symptoms persist or worsen.

Inactive Ingredients
Lactose monohydrate (milk), magnesium stearate, sodium carboxymethylcellulose, xylitol

Directions

Tip bottle silghtly allowing for tablets to fall into the cap.

Use cap to drop tablets into mouth and allow them to dissolve under the tongue.

Adults and children (12 years and older): Take 1 to 4 tablets, one to four times daily, or as recommended by your
healthcare practitioner.

Children (under 12 years): Take under the direction of your healthcare practitioner.

Uses

for the temporary relief from mild acne and brittle nails.

Directions

Tip bottle slightly allowing for tablets to fall into cap.

Use cap to drop tablets into mouth and allow them to dissolve under the tongue.

Adults and Adolescents (12 years and older): Take 1 to 4 tablets, one to four times daily, or as recommended by your healthcare practitioner.

Children (under 12 years): Take under the direction of your healthcare practitioner.

Other information
Do not use if seal is missing or
broken.
Store in a cool, dry place.
Contents may not fill package in order
to accommodate required labeling.
Please rely on stated quantity.

PACKAGE LABEL

NDC 62106-1061-2

UNDA
tissue salt
SILICEA 6X
Homeopathic Remedy
Cell Salt

For the temporary relief from mild acne and brittle nails.
100 Tablets